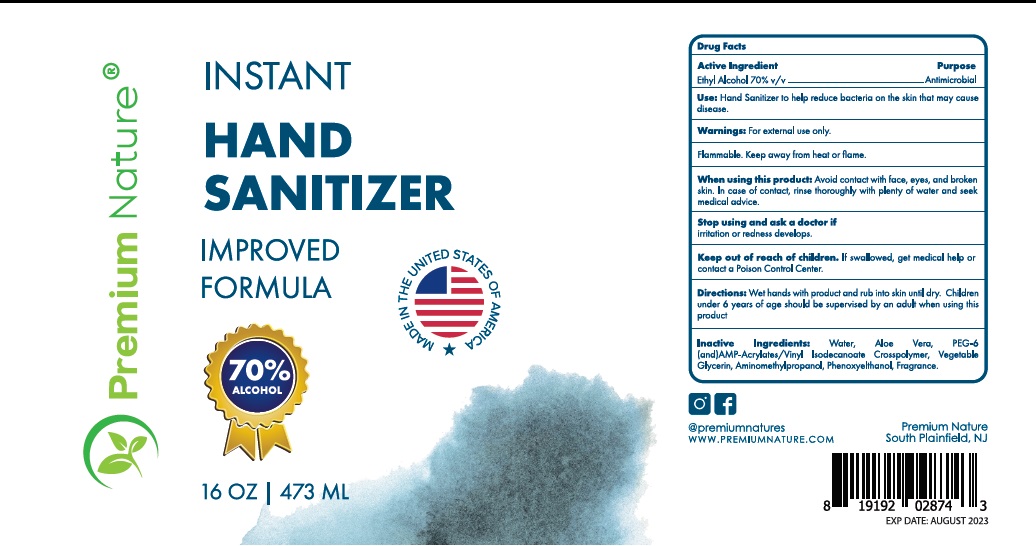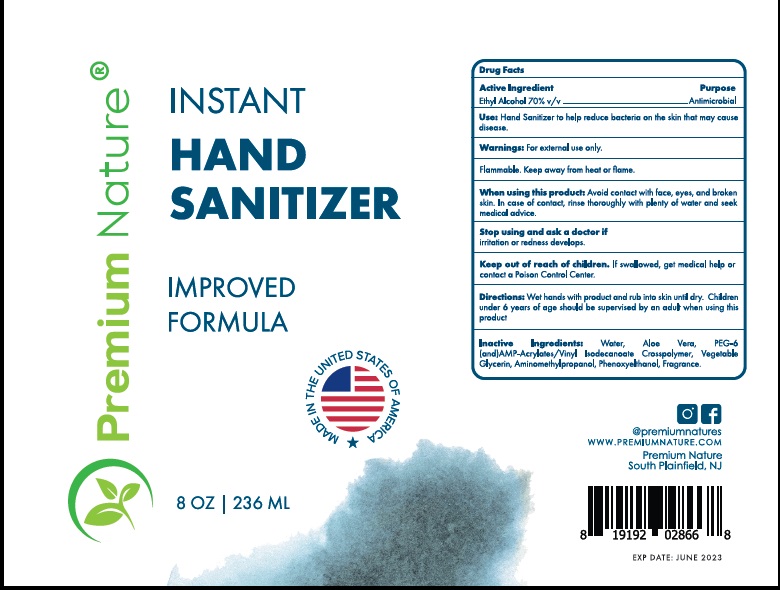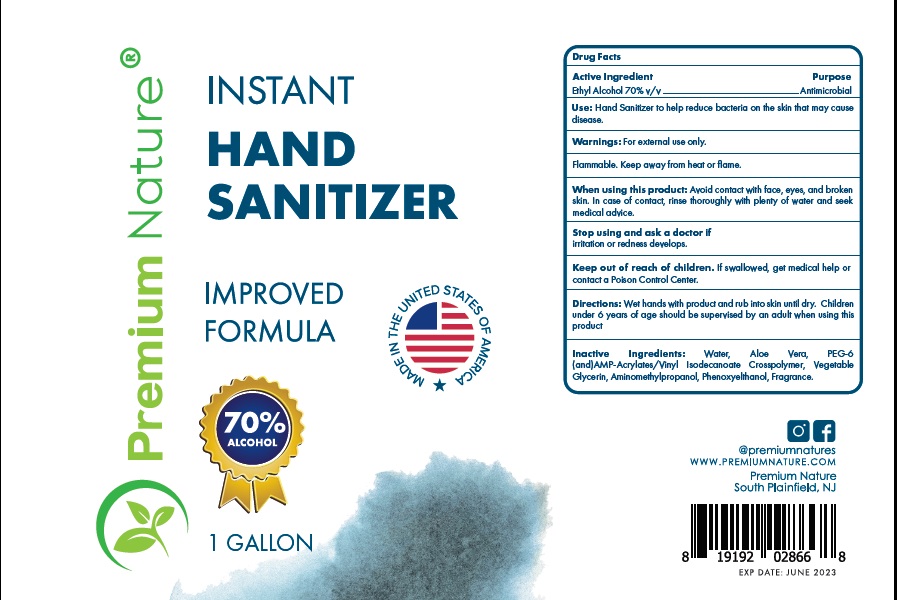 DRUG LABEL: Premium Nature Instant hand sanitizer
NDC: 75821-002 | Form: GEL
Manufacturer: Premium Assure Inc
Category: otc | Type: HUMAN OTC DRUG LABEL
Date: 20210205

ACTIVE INGREDIENTS: ALCOHOL 70 mL/100 mL
INACTIVE INGREDIENTS: ALOE VERA LEAF; WATER; POLYETHYLENE GLYCOL 300; AMINOMETHYLPROPANOL; PHENOXYETHANOL; GLYCERIN

ACTIVE INGREDIENT

Ethyl Alcohol 70%

PURPOSE

Antiseptic hand sanitizer

USES

For hand sanitizing to decrease bacteria on skin

Recommended for repeated use

WARNINGS

For external use only. Flammable. Keep away from fire or flame.

When using this product: Avoid contact with eyes.In case of eye contact, flush eyes with water.

Stop use and ask a doctor if: irritation or redness develops,or if condition persists for more than 72 hours.

KEEP OUT OF REACH OF CHILDREN

If swallowed get medical help or contact a Poison Control Center right away.

DIRECTIONS

Squeeze appropriate amount of sanitizer on to hands and rub together until dry.

Use as needed. For children under 6, use with adult supervision. Not recommended for infants.

INACTIVE INGREDIENTS

Water, Aloe vera, PEG-6 (and) AMP-Acrylates /Vinyl Isodecanoate Crosspolymer, Vegatable Glycerin, Aminomethylpropanol, Phenoxyethanol, Fragrance